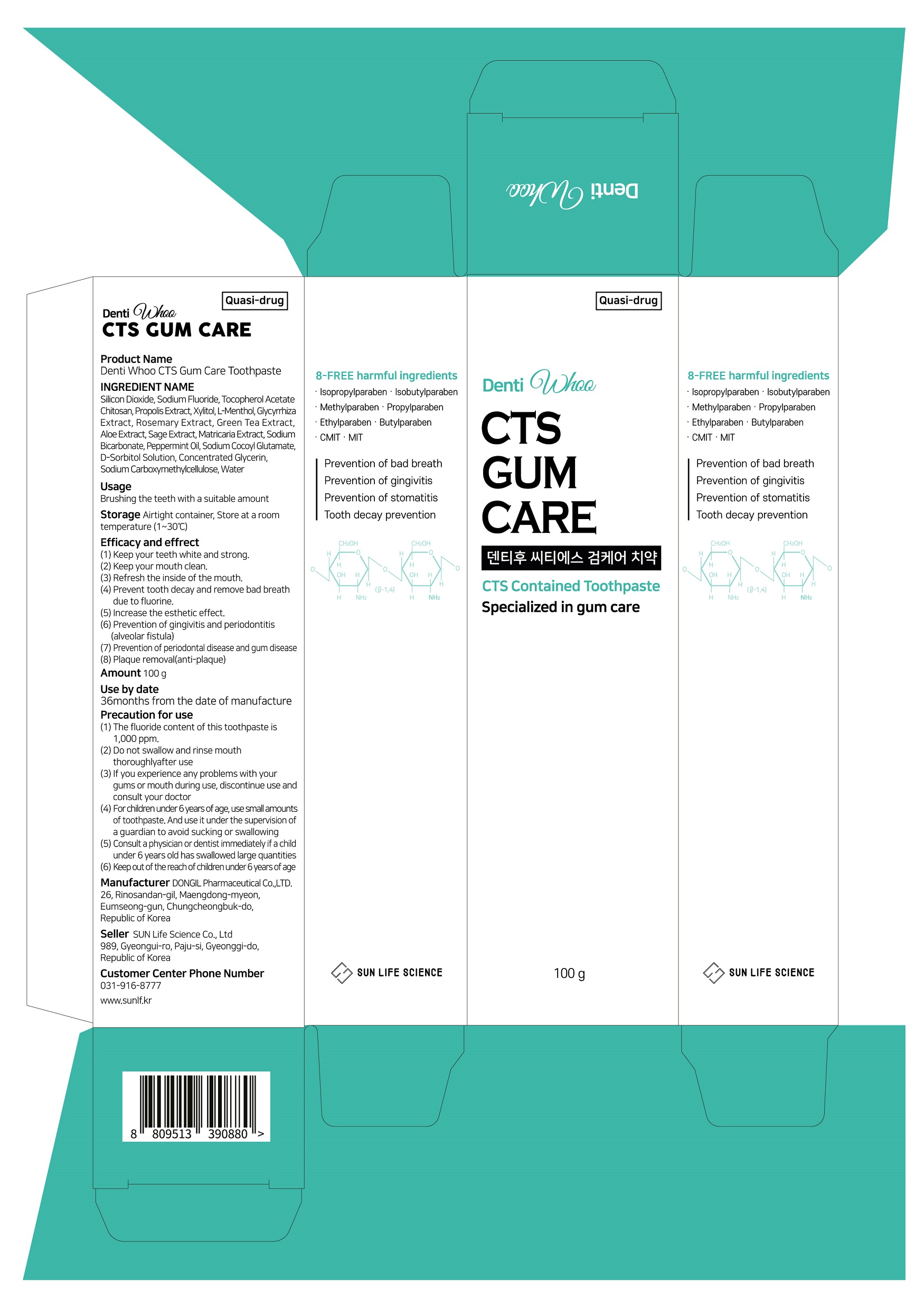 DRUG LABEL: Denti Whoo CTS Gum CareToothpaste
NDC: 86157-0005 | Form: PASTE, DENTIFRICE
Manufacturer: SUN LIFE SCIENCE CO LTD
Category: otc | Type: HUMAN OTC DRUG LABEL
Date: 20220525

ACTIVE INGREDIENTS: SODIUM FLUORIDE 0.22 g/100 g; SILICON DIOXIDE 15 g/100 g; .ALPHA.-TOCOPHEROL ACETATE 0.2 g/100 g
INACTIVE INGREDIENTS: XYLITOL; WATER; LEVOMENTHOL

ACTIVE INGREDIENT

Silicon Dioxide, Sodium Fluoride, Tocopherol Acetate

INACTIVE INGREDIENT

Chitosan, Propolis Extract,Xylitol, L-Menthol, Glycyrrhiza Extract, Rosemary Extract, Green Tea Extract, AloeExtract, Sage Extract, Matricaria Extract, Sodium Bicarbonate, Peppermint Oil, SodiumCocoyl Glutamate, D-Sorbitol Solution, Concentrated Glycerin, SodiumCarboxymethylcellulose, Water

PURPOSE

(1) Keep your teeth white and strong.(2) Keep your mouth clean.(3) Refresh the inside of the mouth.(4) Prevent tooth decay and remove bad breath due to fluorine.(5) Increase the esthetic effect.(6) Prevention of gingivitis and periodontitis(alveolar fistula)(7) Prevention of periodontal disease and gum disease(8) Plaque removal(anti-plaque)

Keep out of reach of children

INDICATIONS AND USAGE

Brushing the teeth with a suitable amount

WARNINGS

(1) The fluoride content of this toothpaste is 1,000 ppm.(2) Do not swallow and rinse mouth thoroughly after use(3) If you experience any problems with your gums or mouth during use,discontinue use and consult your doctor(4) For children under 6 years of age, use small amounts of toothpaste. And use itunder the supervision of a guardian to avoid sucking or swallowing(5) Consult a physician or dentist immediately if a child under 6 years old hasswallowed large quantities(6) Keep out of the reach of children under 6 years of age

DOSAGE AND ADMINISTRATION

For dental use only